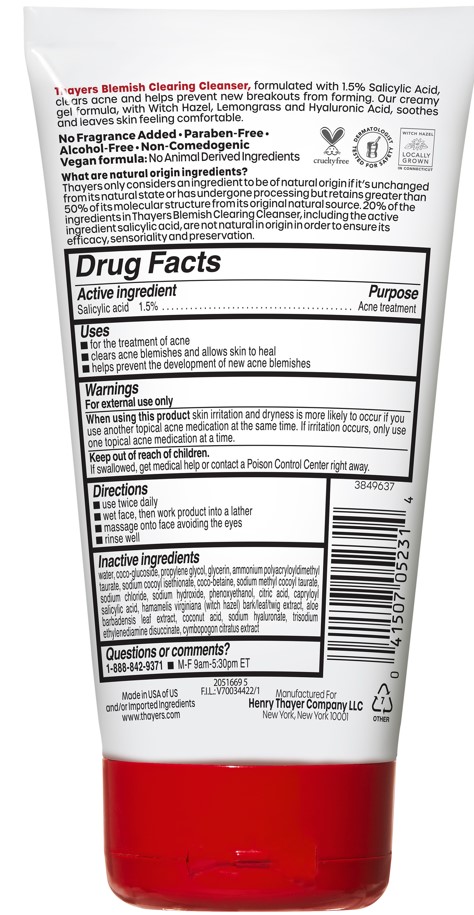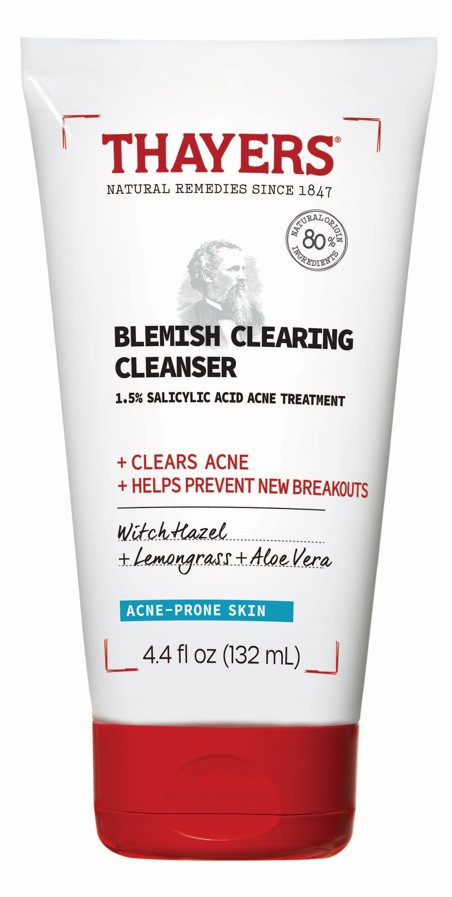 DRUG LABEL: Thayers Natural Remedies Since 1847 Blemish Clearing Cleanser
NDC: 49967-070 | Form: LOTION
Manufacturer: L’Oreal USA Products Inc
Category: otc | Type: HUMAN OTC DRUG LABEL
Date: 20241223

ACTIVE INGREDIENTS: SALICYLIC ACID 15 mg/1 mL
INACTIVE INGREDIENTS: WATER; COCO-GLUCOSIDE; PROPYLENE GLYCOL; GLYCERIN; AMMONIUM POLYACRYLOYLDIMETHYL TAURATE; SODIUM COCOYL ISETHIONATE; COCO-BETAINE; SODIUM METHYL COCOYL TAURATE; SODIUM CHLORIDE; SODIUM HYDROXIDE; PHENOXYETHANOL; CITRIC ACID; CAPRYLOYL SALICYLIC ACID; COCONUT ACID; SODIUM HYALURONATE; TRISODIUM ETHYLENEDIAMINE DISUCCINATE

Drug Facts

Active ingredient

Salicylic acid 1.5%

Purpose

Acne treatment

Uses

- for the treatment of acne
- clears acne blemishes and allows skin to heal
- helps prevent the development of new acne blemishes

Warnings

For external use only

When using this product

skin irritation and dryness is more likely to occur if you use another topical acne medication at the same time. If irritation occurs, only use one topical acne medication at a time.

Keep out of reach of children.

If swallowed, get medical help or contact a Poison Control Center right away.

Directions

- use twice daily
- wet face, then work product into a lather
- massage onto face avoiding the eyes
- rinse well

Inactive ingredients

water, coco-glucoside, propylene glycol, glycerin, ammonium polyacryldimethyl taurate, sodium cocoyl isethionate, coco-betaine, sodium methyl cocoyl taurate, sodium chloride, sodium hydroxide, phenoxyethanol, citric acid, capryloyl salicylic acid, hamamelis virginiana (witch hazel) bark/leaf/twig extract, aloe barbadensis leaf extract, coconut acid, sodium hyaluronate, trisodium ethylenediamine disuccinate, cymbopogon citratus extract

Questions or comments?

1-888-842-9371 M-F 9am-5:30pm ET